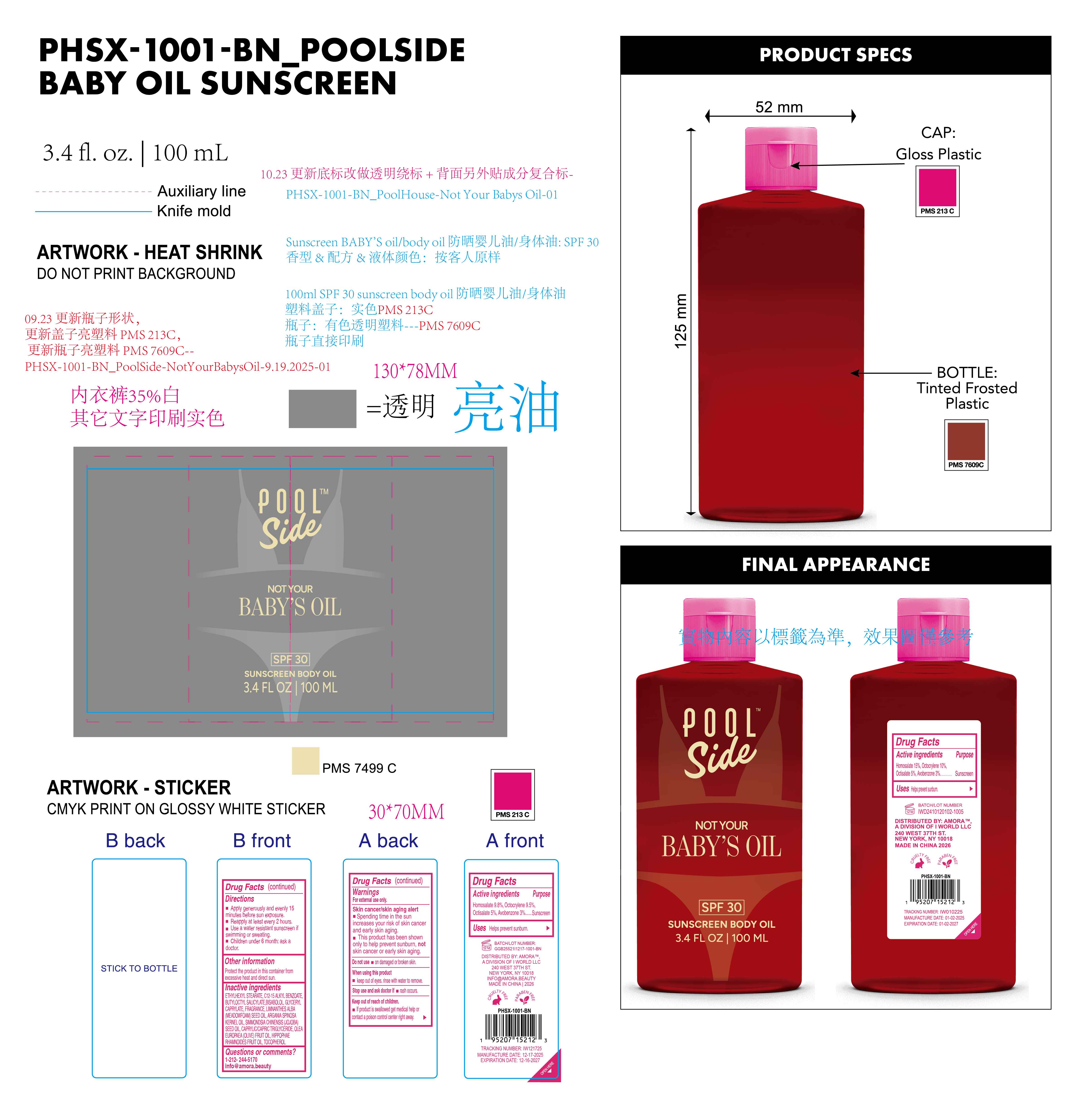 DRUG LABEL: Poolside Not Your Babys Oil. SPF 30 sunscreen body oil.
NDC: 85161-164 | Form: OIL
Manufacturer: Longway Technology(Guangzhou)Co.,Ltd.
Category: otc | Type: HUMAN OTC DRUG LABEL
Date: 20251204

ACTIVE INGREDIENTS: AVOBENZONE 0.028 g/1 mL; OCTISALATE 0.049 g/1 mL; HOMOSALATE 0.098 g/1 mL; OCTOCRYLENE 0.095 g/1 mL
INACTIVE INGREDIENTS: FRAGRANCE 13576; TOCOPHEROL; CAPRYLIC/CAPRIC TRIGLYCERIDE; ARGANIA SPINOSA KERNEL OIL; SIMMONDSIA CHINENSIS (JOJOBA) SEED OIL; HIPPOPHAE RHAMNOIDES FRUIT OIL; GLYCERYL CAPRYLATE; BUTYLOCTYL SALICYLATE; BISABOLOL; ETHYLHEXYL STEARATE; C12-15 ALKYL BENZOATE; OLEA EUROPAEA (OLIVE) FRUIT OIL; LIMNANTHES ALBA (MEADOWFOAM) SEED OIL

ACTIVE INGREDIENT

Homosalate 9.8%, Octocrylene 9.5%, Octisalate 5% , Avobenzone 3%

PURPOSE

Sunscreen

QUESTIONS

1-212- 244-5170 I info @amora.beauty

DOSAGE AND ADMINISTRATION

Apply generously and evenly 15minutes before sun exposure.

Reapply at least every 2 hours.

Use a water resistant sunscreen if swimming or sweating.

Children under 6 month: ask adoctor.

OTHER SAFETY INFORMATION

Protect the product in this container from excessive heat and direct sun.

KEEP OUT OF REACH OF CHILDREN

lf product is swallowed get medical help or contact a poison control center night away.

WARNINGS

For external use only.

Skin cancer/skin aging alert

Spending time in the sun increases your risk of skin cancer and early skin aging.

This product has been shown only to help prevent sunburn, not skin cancer or early skin aging.

Do not use on damaged or broken skin,

When using this product keep out of eyes. rinse with water to remove

Stop use and ask doctor if rash occurs,

Keep out of reach of children.If product is swallowed get medical help or contact a poison control center right away.

INDICATIONS AND USAGE

Helps prevent sunburn.

INACTIVE INGREDIENT

ETHYLHEXYL STEARATE,C12-15 ALKYL BENZOATE,BUTYLOCTYL SALICYLATE,BISABOLOL,GLYCERYL CAPRYLATE,FRAGRANCE,LIMNANTHES ALBA (MEADOWFOAM) SEED OIL,ARGANIA SPINOSA KERNEL OIL,SIMMONDSIA CHINENSIS (JOJOBA) SEED OIL,CAPRYLIC/CAPRIC TRIGLYCERIDE,OLEA EUROPAEA (OLIVE) FRUIT OIL,HIPPOPHAE RHAMNOIDES FRUIT OIL,TOCOPHEROL